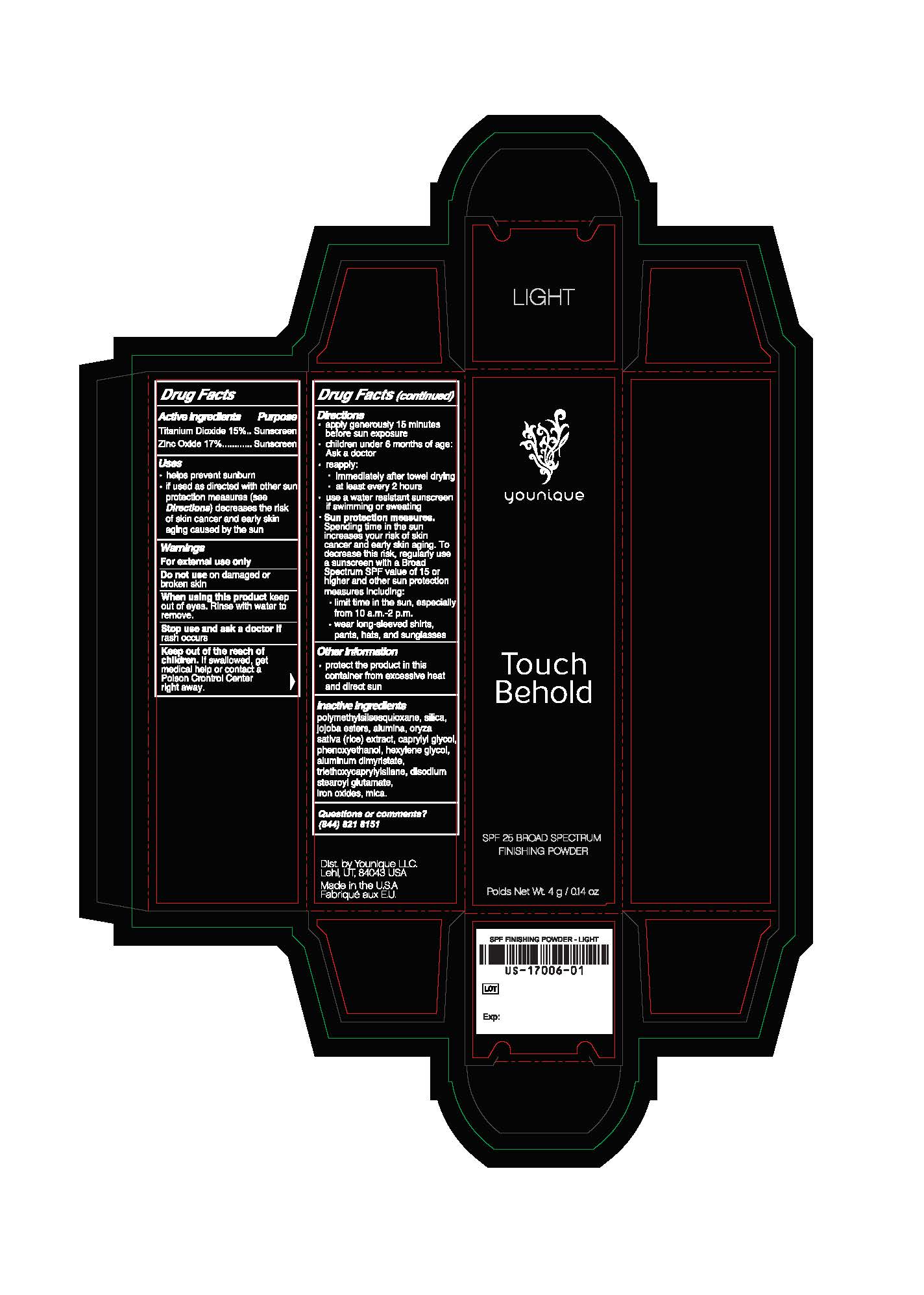 DRUG LABEL: SPF 25 Finishing Powder
NDC: 71182-1706 | Form: POWDER
Manufacturer: Younique LLC
Category: otc | Type: HUMAN OTC DRUG LABEL
Date: 20181012

SPF 25 Finishing Powder

Directions

Apply generously 15 minutes before sun exposure.

Reapply immediately after towel drying.

Reapply at least every 2 hours.

Inactive ingredients

Polymethylsilsesquioxane, Silica, Jojoba Esters, Alumina, Oryza Sativa (Rice) Extract, Caprylyl Glycol, Phenoxyethanol, Hexylene Glycol, Aluminum Dimyristate, Triethoxycaprylylsilane, Disodium Stearoyl Glutamate, Iron Oxides, Mica.

Directions & Uses

Apply generously 15 minutes before sun exposure.

Reapply immediately after towel drying.

Reapply at least every 2 hours.

Helps prevent sunburn.

If used as directed with other sun protection measures decreases the risk of skin cancer and early skin aging caused by the sun.

Warnings

Keep out of reach of children.

Purpose

Sunscreen.

Active ingredients

Titanium Dioxide 15%

Zinc Oxide 17%

Warnings

For external use only

Do not use on damaged or broken skin

When using this product keep out of eyes. Rinse with water to remove

Stop use and ask a doctor if rash occurs

Keep out of reach of children. If swallowed, get medical help or contact a Posion Control Center right away